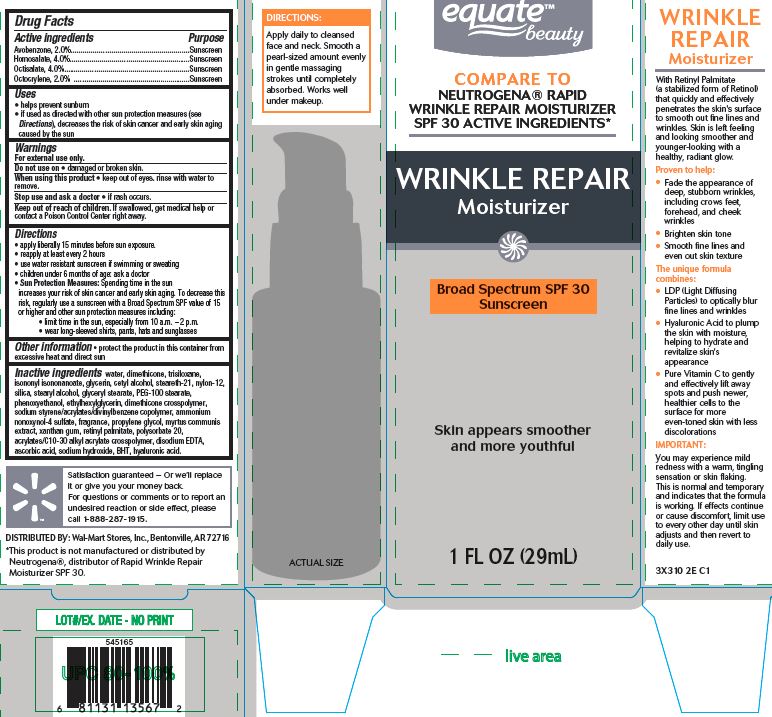 DRUG LABEL: Equate beauty
NDC: 49035-300 | Form: LOTION
Manufacturer: Wal-Mart Stores, Inc
Category: otc | Type: HUMAN OTC DRUG LABEL
Date: 20160419

ACTIVE INGREDIENTS: AVOBENZONE .02 g/29 g; HOMOSALATE .04 g/29 g; OCTISALATE .04 g/29 g; OCTOCRYLENE .02 g/29 g
INACTIVE INGREDIENTS: WATER; DIMETHICONE; TRISILOXANE; ISONONYL ISONONANOATE; GLYCERIN; CETYL ALCOHOL; STEARETH-21; SILICON DIOXIDE; PEG-100 STEARATE; PHENOXYETHANOL; ETHYLHEXYLGLYCERIN; DIMETHICONE CROSSPOLYMER (450000 MPA.S AT 12% IN CYCLOPENTASILOXANE); STYRENE; SODIUM; DIVINYLBENZENE; AMMONIUM NONOXYNOL-4 SULFATE; PROPYLENE GLYCOL; MYRTUS COMMUNIS LEAF; XANTHAN GUM; VITAMIN A PALMITATE; POLYSORBATE 20; ALLYL ACRYLATE; EDETATE DISODIUM; ASCORBIC ACID; SODIUM HYDROXIDE; TRIS-BHT MESITYLENE; HYALURONIC ACID

Active ingredients

Avobenzone 2.0%

Homosalate 4.0%

Octisalate 4.0%

Octocrylene 2.0%

Purpose

Sunscreen

Sunscreen

Sunscreen

Sunscreen

Uses

- helps prevent sunburn

- if used as directed with other sun protection measures (see Directions), decreases the risk of skin cancer and and early aging caused by the sun

Warnings

For external use only.

Do not use on - damaged or broken skin

When using this product - keep out of eyes, rinse with water to remove.

Stop use and ask a doctor - if rash occurs

Keep out of reach of children. If swallowed, get medical help or

contact a Poison Control Center right away.

Directions

- apply liberally 15 minutes before sun exposure

- reapply at least every 2 hours

- use water resistant sunscreen if swimming or sweating

- children under 6 months of age: ask a doctor

- Sun Protection Measures: Spending time in the sun increases your risk of skin cancer and early sking aging. To decrease this risk, regularly use a sunscreen with a Broad Spectrum SPF value of 15 or higher and other sun protection measures including:

-limit time in the sun, especially from 10 a.m. - 2 p.m.

-wear long-sleeved shirts, pants, hats and sunglasses

Other Information - protect the product in this container from excessive heat and direct sun.

INACTIVE INGREDIENT

Inactive Ingredients water, dimethicone, trisiloxane, isononyl isononanoate, glycerin,

cetyl alcohol, steareth-21, nylon-12, silica, stearyl alcohol, glyceryl stearate, PEG-100 stearate,

phenoxyethanol, ethylhexylglycerin, dimethicone crosspolymer, sodium styrene/acrylates/divinylbenzene

copolymer, ammonium nonoxynol-4 sulfate, fragrance, propylene glycol, myrtus communis extract,

xantan gum, retinyl palmitate, polysorbate 20, acrylates/C10-30 alkyl acrylate crosspolymer,

disodium EDTA, ascorbic acid, sodium hydroxide, BHT, hyaluronic acid